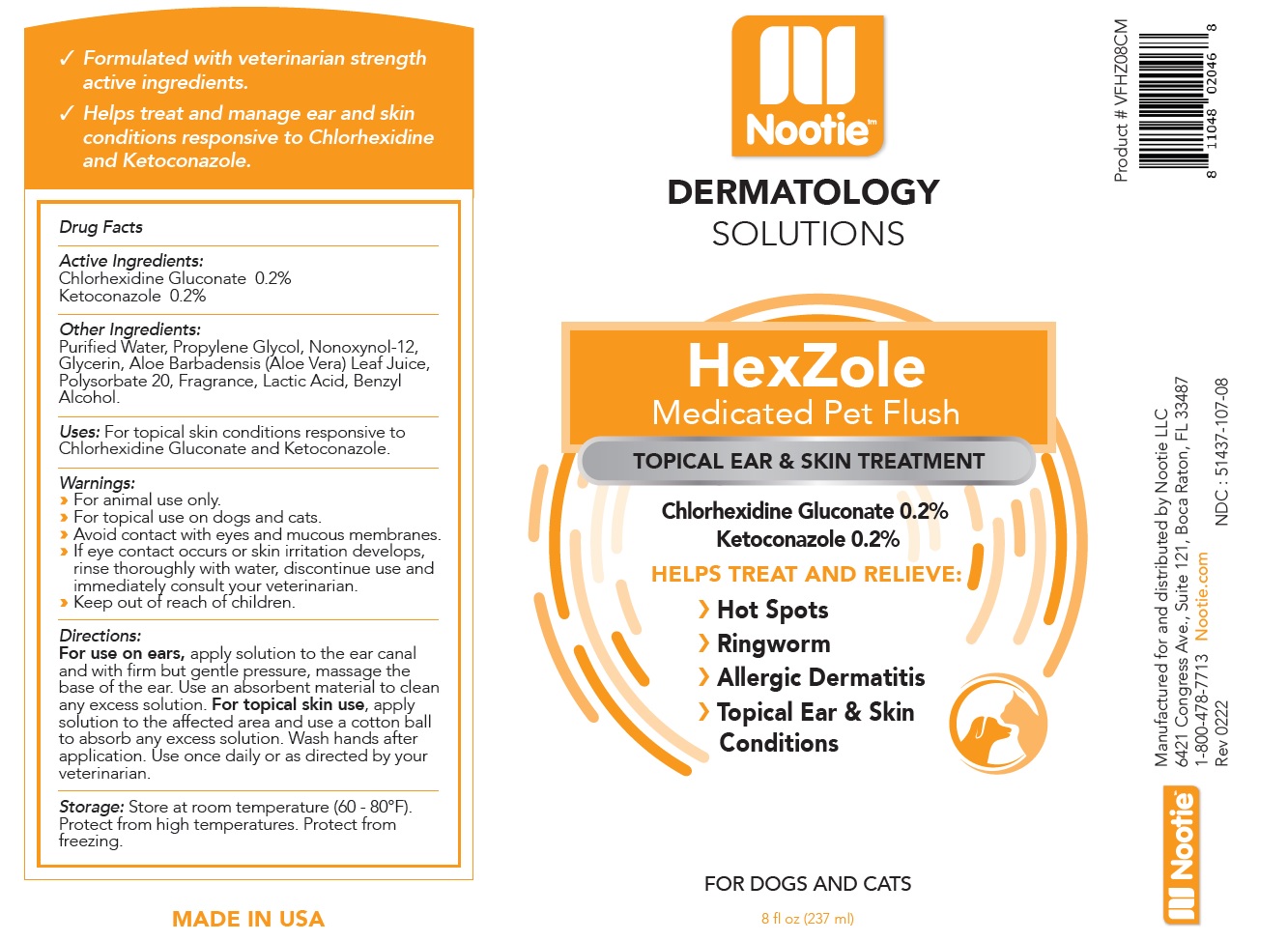 DRUG LABEL: Nootie HexZole Medicated Pet Flush
NDC: 51437-107 | Form: SOLUTION
Manufacturer: Nootie LLC
Category: animal | Type: OTC ANIMAL DRUG LABEL
Date: 20221124

ACTIVE INGREDIENTS: CHLORHEXIDINE GLUCONATE 2 mg/1 mL; KETOCONAZOLE 2 mg/1 mL
INACTIVE INGREDIENTS: WATER; PROPYLENE GLYCOL; NONOXYNOL-12; GLYCERIN; ALOE VERA LEAF; POLYSORBATE 20; LACTIC ACID, UNSPECIFIED FORM; BENZYL ALCOHOL

Nootie™ HexZole Medicated Pet Flush

Active Ingredients:

Chlorhexidine Gluconate 0.2%
Ketoconazole 0.2%

Other Ingredients:

Purified Water, Propylene Glycol, Nonoxynol-12, Glycerin, Aloe Barbadensis (Aloe Vera) Leaf Juice, Polysorbate 20, Fragrance, Lactic Acid, Benzyl Alcohol.

Uses:

For topical skin conditions responsive to Chlorhexidine Gluconate and Ketoconazole.

Warnings:

› For animal use only.
› For topical use on dogs and cats.
› Avoid contact with eyes and mucous membranes.
› If eye contact occurs or skin irritation develops, rinse thoroughly with water, discontinue use and immediately consult your veterinarian.
› Keep out of reach of children.

Directions:

For use on ears, apply solution to the ear canal and with firm but gentle pressure, massage the base of the ear. Use an absorbent material to clean any excess solution. For topical skin use, apply solution to the affected area and use a cotton ball to absorb any excess solution. Wash hands after application. Use once daily or as directed by your veterinarian.

Storage:

Store at room temperature (60 - 80°F). Protect from high temperatures. Protect from freezing.

Nootie™ DERMATOLOGY SOLUTIONS

TOPICAL EAR & SKIN TREATMENT

HELPS TREAT AND RELIEVE:

› Hot Spots
› Ringworm
› Allergic Dermatitis
› Topical Ear & Skin Conditions

FOR DOGS AND CATS

√ Formulated with veterinarian strength active ingredients.
√ Helps treat and manage ear and skin conditions responsive to Chlorhexidine and Ketoconazole.

MADE IN USA

Manufactured for and distributed by Nootie LLC
6421 Congress Ave., Suite 121, Boca Raton, FL 33487
1-800-478-7713 Nootie.com